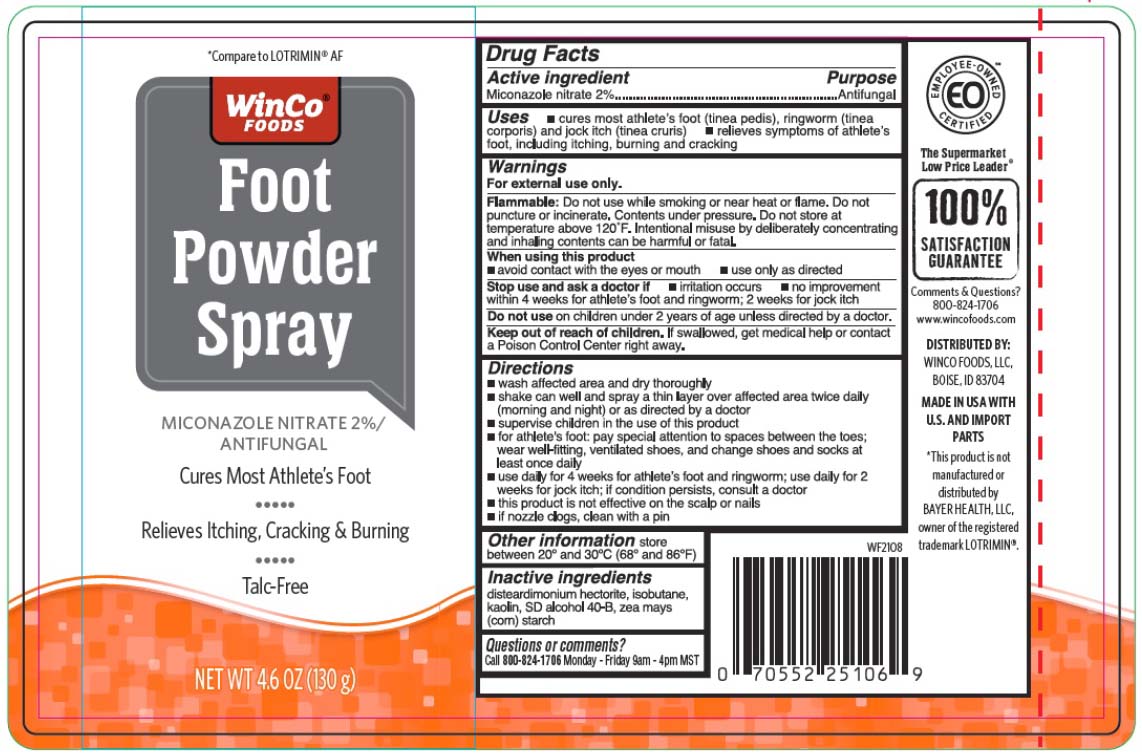 DRUG LABEL: Miconazole Nitrate
NDC: 67091-392 | Form: AEROSOL, SPRAY
Manufacturer: Winco Foods, LLC
Category: otc | Type: HUMAN OTC DRUG LABEL
Date: 20251029

ACTIVE INGREDIENTS: MICONAZOLE NITRATE 2.6 g/130 g
INACTIVE INGREDIENTS: ISOBUTANE; ALCOHOL; DISTEARDIMONIUM HECTORITE; ZEA MAYS SUBSP. MAYS WHOLE; KAOLIN

Winco Antifungal Miconazole Powder Spray

Active ingredient

Miconozole nitrate 2%

Purpose

Antifungal

Uses

- cures most athlete's foot (tinea pedis), ringworm (tinea corporis) and jock itch (tinea cruris)
- relieves symtoms of athlete's foot, including itching, burning and cracking

Warnings

For external use only.

Flammable:

Do not use while smoking or near heat or flame. Do not puncture or incinerate. Contents under pressure. Do not store at temperature above 120°F. Intentional misuse by deliberately concentrationg and inhaling contents can be harmful or fatal.

When using this product

- avoid contact with the eyes or mouth
- use only as directed

Stop use and ask a doctor if

- irritation occurs
- no improvement within 4 weeks for athlete's foot and ringworm; 2 weeks for jock itch

Do not use

on children under 2 years of age unless directed by a doctor.

Keep out of reach of children

If swallowed, get medical help or contact a Poison Control Center right away.

Directions

- wash affected area and dry thoroughly
- shake can well and spray a thin layer over affected area twice daily (morning and night) or as directed by a doctor
- supervise children in the use of this product
- for athlete's foot: pay special attention to spaces between toes; wear well-fitting, ventilated shoes, and change shoes and socks at least once daily
- use daily for 4 weeks for athlete's foot and ringworm; use daily for 2 weeks for jock itch; if condition persists, consult a doctor
- this product is not effective on scalp or nails
- if nozzle clogs, clean with a pin

Other infomation

store between 20o and 30o C (68o and 86oF)

Inactive ingredients

disteardimonium hectorite, isobutane, kaolin, SD alcohol 40-B, zea mays (corn) starch

Questions

Call 800-824-1706 Monday - Friday 9 am - 4pm MST

PRINCIPAL DISPLAY PANEL

Foot Powder Spray

Miconazole Nitrate 2%/

ANTIFUNGAL

Cures Most Athelete's Foot

Relieves Itching, Cracking and Burning

Talc Free

NET WT 4.6 OZ (130g)